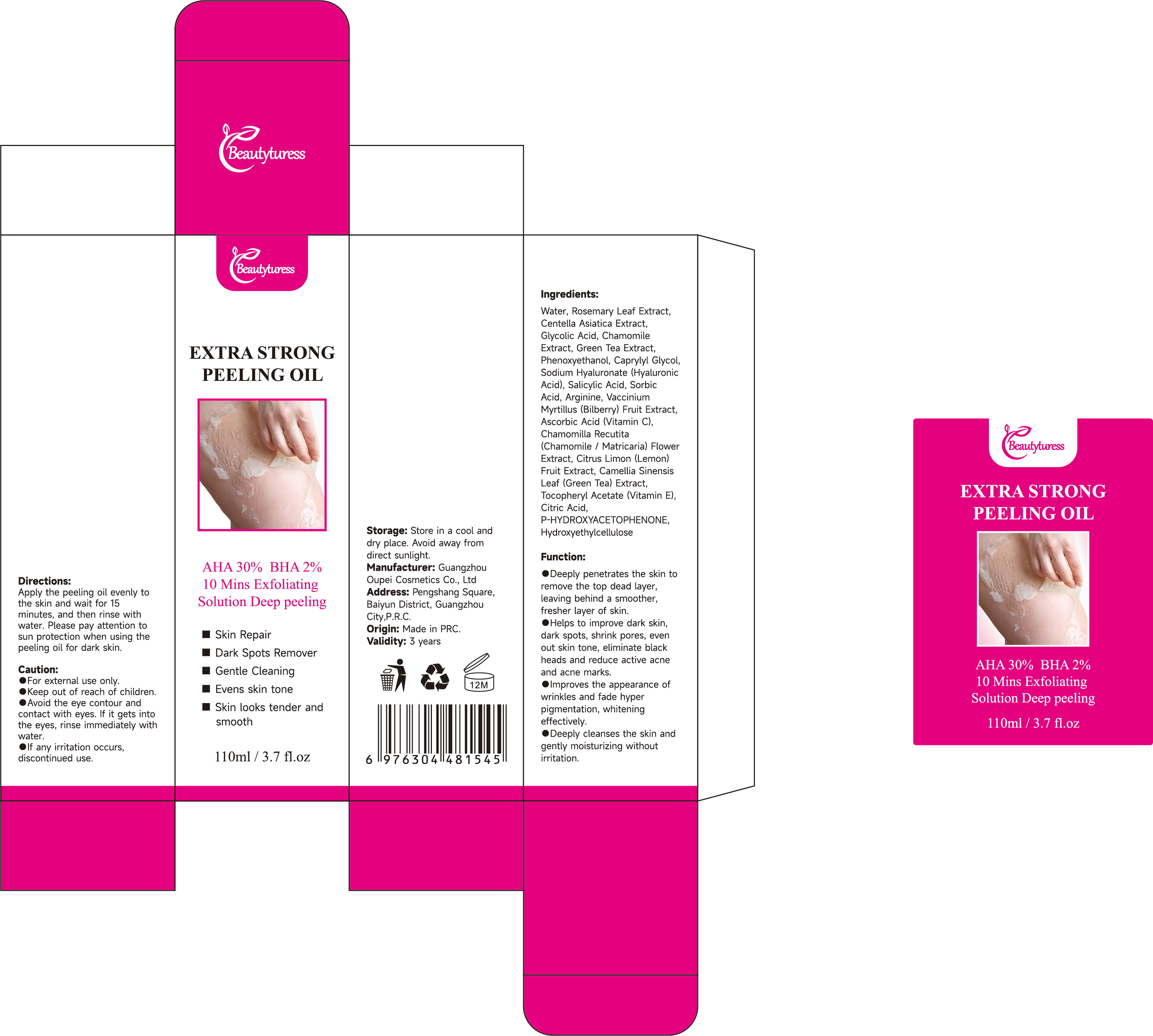 DRUG LABEL: Beautyturess Exfoliating Peeling Oil
NDC: 84753-006 | Form: EMULSION
Manufacturer: Guangdong Bisutang Biotechnology Co., Ltd.
Category: otc | Type: HUMAN OTC DRUG LABEL
Date: 20241014

ACTIVE INGREDIENTS: 3-O-ETHYL ASCORBIC ACID 0.055 g/110 mL
INACTIVE INGREDIENTS: POLYOXYL 40 HYDROGENATED CASTOR OIL; SCUTELLARIA BAICALENSIS ROOT; ROSMARINUS OFFICINALIS WHOLE; DIPROPYLENE GLYCOL; WATER; .ALPHA.-TOCOPHEROL; CAMELLIA SINENSIS ROOT; CETYL HYDROXYETHYLCELLULOSE (350000 MW); CENTELLA ASIATICA; POLYGONUM CUSPIDATUM ROOT; METHYLPARABEN; METHOXY PEG-100; GLYCYRRHIZA GLABRA; DIAZOLIDINYL UREA; BUTYLENE GLYCOL 1-CAPRATE 3-CAPRYLATE; DIGLYCERIN; MATRICARIA CHAMOMILLA LEAF

ACTIVE INGREDIENT

3-o-ETHYL ASCORBIC ACID---0.055g

PURPOSE

1. Removes Dead Skin Cells
Exfoliating peeling oil helps dissolve and peel away dead skin cells on the surface of the skin, promoting cell turnover and leaving the skin smoother and more radiant.
2. Enhances Absorption
After exfoliation, the skin’s surface is free from obstructions, allowing it to better absorb active ingredients from subsequent skincare products such as serums and moisturizers, boosting their effectiveness.

Ask Doctor

If you have a history of skin allergies or have sensitive skin, it is advisable to consult a doctor before using this product.

DOSAGE AND ADMINISTRATION

Apply once daily to clean face and neck, avoiding the eye area

WHEN USING

Avoid contact with eyes and broken skin. If redness, swelling, or irritation occurs, discontinue use immediately and seek medical advice.

WARNINGS

Risk InformationFor external use only
Mention de risquesPour usage externe seulement
Do not use on damaged or broken skin.
Ne pas utiliser sur la peau endommagée ou avec des lésions
If rash occurs, discontinue use and consult a health care practitioner.
En présence d'une éruption cutanée, cesser l'utilisation et consulter un praticien de soins de santé
When using this product keep out of eyes. Rinse with water to remove.
Eviter tout contact avec les yeux. Rincer a l'eau le cas échéant
Keep out of reach of children. If swallowed, get medical help or contact a Poison Control Center right away.
Tenir hors de portée des enfants
En cas d'ingestion, consulter un médecin ou appeler un centre antipoison immédiatement.

INDICATIONS AND USAGE

1. Removes Dead Skin Cells
Exfoliating peeling oil helps dissolve and peel away dead skin cells on the surface of the skin, promoting cell turnover and leaving the skin smoother and more radiant.
2. Enhances Absorption
After exfoliation, the skin’s surface is free from obstructions, allowing it to better absorb active ingredients from subsequent skincare products such as serums and moisturizers, boosting their effectiveness.

Keep out of reach of children. If swallowed, get medical help or contact a Poison Control Center right away.
Tenir hors de portée des enfants
En cas d'ingestion, consulter un médecin ou appeler un centre antipoison immédiatement.

INACTIVE INGREDIENT

AQUA
POLYVINYL ALCOHOL
ALCOHOL
PHENOXYETHANOL
CARBOMER
TRIETHANOLAMINE
METHYLPARABEN
PEG-40 HYDROGENATED CASTOR OIL
TITANIUM DIOXIDE
ALUMINA
SILICA
FRAGRANCE
CI 19140
SODIUM CHLORIDE
CI 15985
BUTYLENE GLYCOL
PHENOXYETHANOL